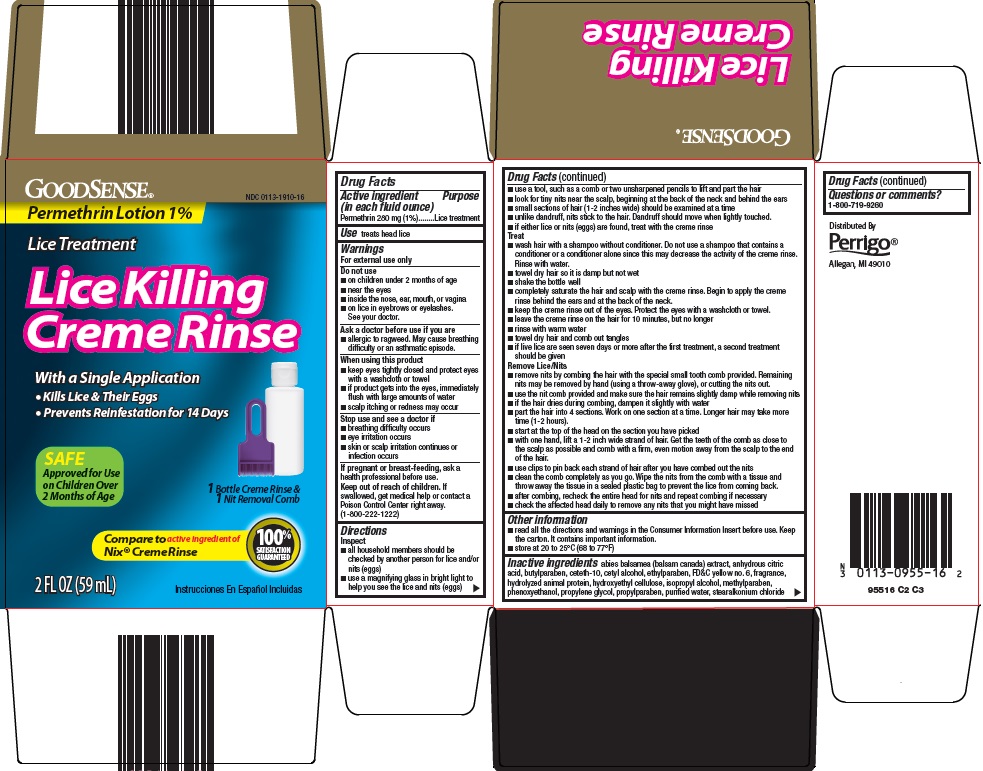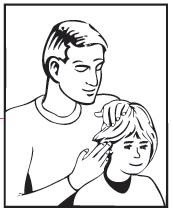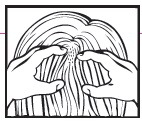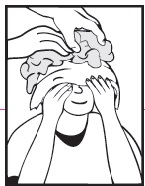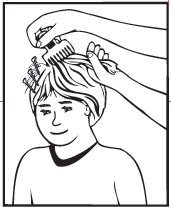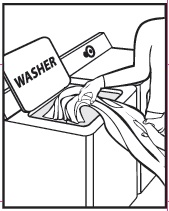 DRUG LABEL: good sense lice killing creme rinse
NDC: 0113-1910 | Form: LOTION
Manufacturer: L. Perrigo Company
Category: otc | Type: HUMAN OTC DRUG LABEL
Date: 20221121

ACTIVE INGREDIENTS: PERMETHRIN 1 mg/100 mL
INACTIVE INGREDIENTS: BALSAM FIR LEAFY TWIG; ANHYDROUS CITRIC ACID; BUTYLPARABEN; CETETH-10; CETYL ALCOHOL; ETHYLPARABEN; FD&C YELLOW NO. 6; ISOPROPYL ALCOHOL; METHYLPARABEN; PHENOXYETHANOL; PROPYLENE GLYCOL; PROPYLPARABEN; WATER; STEARALKONIUM CHLORIDE

Perrigo Lice Killing Creme Rinse Drug Facts

Active ingredient (in each fluid ounce)

Permethrin 280 mg (1%)

Purpose

Lice treatment

Use

treats head lice

Warnings

For external use only

Do not use

1. on children under 2 months of age
2. near the eyes
3. inside the nose, ear, mouth, or vagina
4. on lice in eyebrows or eyelashes.

See your doctor.

Ask a doctor before use if you are

1. allergic to ragweed. May cause breathing difficulty or an asthmatic episode.

When using this product

1. keep eyes tightly closed and protect eyes with a washcloth or towel
2. if product gets into the eyes, immediately flush with large amounts of water
3. scalp itching or redness may occur

Stop use and see a doctor if

1. breathing difficulty occurs
2. eye irritation occurs
3. skin or scalp irritation continues or infection occurs

If pregnant or breast-feeding,

ask a health professional before use.

Keep out of reach of children.

If swallowed, get medical help or contact a Poison Control Center right away. (1-800-222-1222)

Directions

Inspect

1. all household members should be checked by another person for lice and/or nits (eggs)
2. use a magnifying glass in bright light to help you see the lice and nits (eggs)
3. use a tool, such as a comb or two unsharpened pencils to lift and part the hair
4. look for tiny nits near the scalp, beginning at the back of the neck and behind the ears
5. small sections of hair (1-2 inches wide) should be examined at a time
6. unlike dandruff, nits stick to the hair. Dandruff should move when lightly touched.
7. if either lice or nits (eggs) are found, treat with the creme rinse

Treat

1. wash hair with a shampoo without conditioner. Do not use a shampoo that contains a conditioner or a conditioner alone since this may decrease the activity of the creme rinse. Rinse with water.
2. towel dry hair so it is damp but not wet
3. shake the bottle well
4. completely saturate the hair and scalp with the creme rinse. Begin to apply the creme rinse behind the ears and at the back of the neck.
5. keep the creme rinse out of the eyes. Protect the eyes with a washcloth or towel.
6. leave the creme rinse on the hair for 10 minutes, but no longer
7. rinse with warm water
8. towel dry hair and comb out tangles
9. if live lice are seen seven days or more after the first treatment, a second treatment should be given

Remove Lice/Nits

1. remove nits by combing the hair with the special small tooth comb provided. Remaining nits may be removed by hand (using a throw-away glove), or cutting the nits out.
2. use the nit comb provided and make sure the hair remains slightly damp while removing nits
3. if the hair dries during combing, dampen it slightly with water
4. part the hair into 4 sections. Work on one section at a time. Longer hair may take more time (1-2 hours).
5. start at the top of the head on the section you have picked
6. with one hand, lift a 1-2 inch wide strand of hair. Get the teeth of the comb as close to the scalp as possible and comb with a firm, even motion away from the scalp to the end of the hair.
7. use clips to pin back each strand of hair after you have combed out the nits
8. clean the comb completely as you go. Wipe the nits from the comb with a tissue and throw away the tissue in a sealed plastic bag to prevent the lice from coming back.
9. after combing, recheck the entire head for nits and repeat combing if necessary
10. check the affected head daily to remove any nits that you might have missed

Other information

1. read all the directions and warnings in the Consumer Information Insert before use. Keep the carton. It contains important information.
2. store at 20 to 25°C (68 to 77°F)

Inactive ingredients

abies balsamea (balsam canada) extract, anhydrous citric acid, butylparaben, ceteth-10, cetyl alcohol, ethylparaben, FD&C yellow no. 6, fragrance, hydrolyzed animal protein, hydroxyethyl cellulose, isopropyl alcohol, methylparaben, phenoxyethanol, propylene glycol, propylparaben, purified water, stearalkonium chloride

Questions or comments?

1-800-719-9260

Consumer Information

Permethrin Lotion, 1%

Lice Treatment Creme Rinse

THE FACTS OF LICE

Please read all information before using Lice Treatment Creme Rinse.

If you or a member of your household has head lice, don’t panic. Keep calm.

Anyone can get head lice - it has nothing to do with cleanliness or poor hygiene. Head lice are treatable and very rarely cause serious health problems.

What are head lice?

1. head lice are small insects that live and feed on the human scalp
2. they may get as big as sesame seeds and are brown
3. lice do not fly or jump from one person to another. They can only crawl.

What are nits?

1. nits are lice eggs laid on the hair near the scalp. One louse may lay over 100 nits.
2. nits are oval shaped, tiny and greyish-white
3. they are attached to hair with a waterproof glue-like substance that cannot be washed out or blown away

Because nits (eggs) hatch in about one week, all nits must be removed to stop lice.

How do head lice spread?

1. head lice spread easily from close head-to-head or hand-to-head contact with persons who have lice
2. they may also spread by sharing hats, helmets, scarves, headphones, brushes, combs, bedding and clothing

How do you know if you have lice?

1. itching is the most common symptom
2. scratching behind the ears or the back of the neck is a sign that you should check for head lice
3. scabs or blood spots may be seen

How do you prevent the spread of lice?

1. do not share or borrow personal items like combs, brushes, or headbands
2. do not share or borrow hats, sweaters, coats, scarves, helmets, headphones, pillows or stuffed animals
3. store hats in coat sleeves and hang coats separately, so that they do not touch other people’s hats and coats
4. wash under fingernails when you first see lice or nits (eggs)
5. check your child’s head daily when you hear of a lice outbreak in day care or school

How to use the creme rinse

I. Inspect

If you suspect head lice - check. Head lice may be hard to locate because they avoid light. Nits are easier to see.

- all household members should be checked by another person for lice and/or nits (eggs)
- use a magnifying glass in bright light to help you see the lice and nits (eggs)
- use a tool, such as a comb or two unsharpened pencils to lift and part the hair
- look for tiny nits near the scalp, beginning at the back of the neck and behind the ears
- small sections of hair (1-2 inches wide) should be examined at a time
- unlike dandruff, nits stick to the hair. Dandruff should move when lightly touched.
- if either lice or nits (eggs) are found, treat with the creme rinse

II. Treat

1. wash hair with a shampoo without conditioner. Do not use a shampoo that contains a conditioner or a conditioner alone since this may decrease the activity of the creme rinse. Rinse with water.
2. towel dry hair so it is damp but not wet
3. shake the bottle well
4. completely saturate the hair and scalp with the creme rinse. Begin to apply the creme rinse behind the ears and at the back of the neck.
5. keep the creme rinse out of the eyes. Protect the eyes with a washcloth or towel.
6. leave the creme rinse on the hair for 10 minutes, but no longer
7. rinse with warm water
8. towel dry hair and comb out tangles
9. if live lice are seen seven days or more after the first treatment, a second treatment should be given

III. Remove Lice/Nits

Treatment kills lice but does not remove the nits.

1. remove nits by combing the hair with the special small tooth comb provided. Remaining nits may be removed by hand (using a throw-away glove), or cutting the nits out.
2. use the nit comb provided and make sure the hair remains slightly damp while removing nits
3. if the hair dries during combing, dampen it slightly with water
4. part the hair into 4 sections. Work on one section at a time. Longer hair may take more time (1-2 hours).
5. start at the top of the head on the section you have picked
6. with one hand, lift a 1-2 inch wide strand of hair. Get the teeth of the comb as close to the scalp as possible and comb with a firm, even motion away from the scalp to the end of the hair.
7. use clips to pin back each strand of hair after you have combed out the nits
8. clean the comb completely as you go. Wipe the nits from the comb with a tissue and throw away the tissue in a sealed plastic bag to prevent the lice from coming back.
9. after combing, recheck the entire head for nits and repeat combing if necessary
10. check the affected head daily to remove any nits that you might have missed

IV. Clean home and personal items

After using the creme rinse, it is very important to clean personal items and your home to prevent the spread of lice. Nits may live away from the human head for about 7-12 days. Lice may live away from the human head for about 1 day.

1. all personal head gear (hats, hair ribbons, etc.), scarves, coats, towels and bed linens should be washed in hot water (above 130°F), then dried in the dryer using the hottest cycle for at least 20 minutes
2. personal combs, including nit combs, and brushes should be soaked in hot water (above 130°F) for at least 10 minutes
3. personal articles such as clothing, bedspreads, blankets, pillows or stuffed animals that cannot be washed should be dry-cleaned or sealed tightly in a plastic bag for a period of at least 4 weeks. Items should be taken out of the plastic bag outdoors and shaken out very hard before using again.
4. for anything you cannot wash, dry-clean or store in a plastic bag, spray with lice control spray.
5. vacuum everywhere. Vacuum all carpets, mattresses, upholstered furniture and car seats that may have been used by infested household members.

Warnings

For external use only

Do not use

1. on children under 2 months of age
2. near the eyes
3. inside the nose, ear, mouth, or vagina
4. on lice in eyebrows or eyelashes. See your doctor.

Ask a doctor before use if you are

1. allergic to ragweed. May cause breathing difficulty or an asthmatic episode.

When using this product

1. keep eyes tightly closed and protect eyes with a washcloth or towel
2. if product gets into the eyes, immediately flush with large amounts of water
3. scalp itching or redness may occur

Stop use and see a doctor if

1. breathing difficulty occurs
2. eye irritation occurs
3. skin or scalp irritation continues or infection occurs

If pregnant or breast-feeding,

ask a health professional before use.

Keep out of reach of children.

If swallowed, get medical help or contact a Poison Control Center right away. (1-800-222-1222)

Question or comments?

1-800-719-9260

Distributed By

Perrigo®

Allegan, MI 49010

:95500 00 J2

Principal Display Panel

Permethrin Lotion 1%

Lice Treatment

Lice Killing Creme Rinse

With a Single Application

Kills Lice & Their Eggs

Prevents Reinfestation for 14 Days

SAFE

Approved for Use on Children Over 2 Months of Age

1 Bottle Creme Rinse & 1 Nit Removal Comb

Compare to active ingredient of Nix® Creme Rinse

100% SATISFACTION GUARANTEED

2 FL OZ (59 mL)